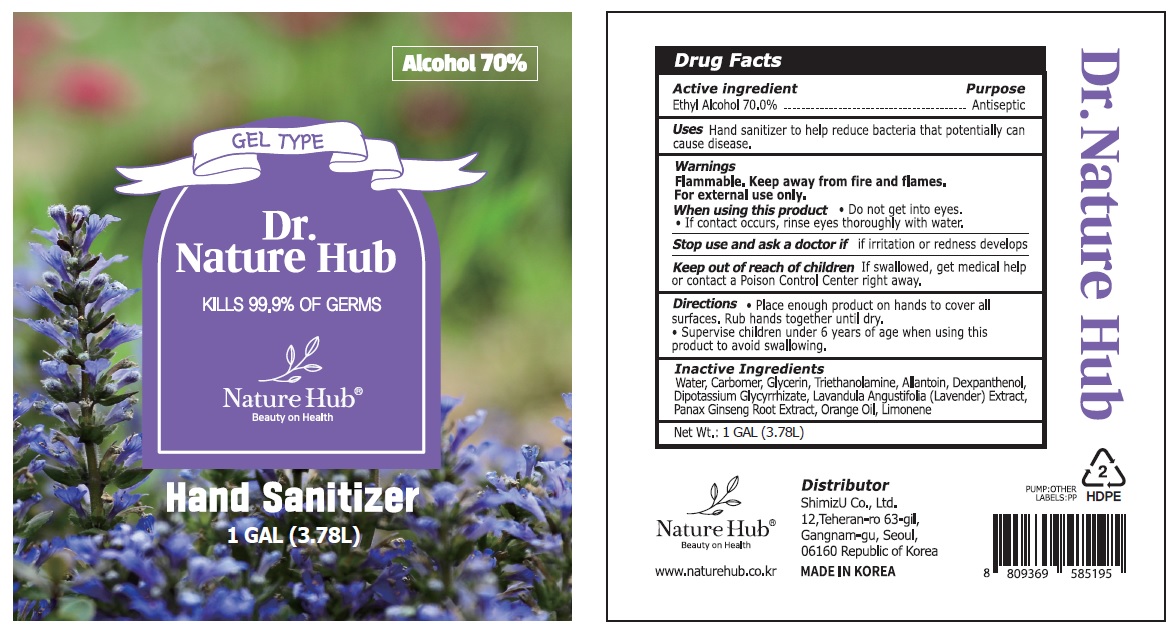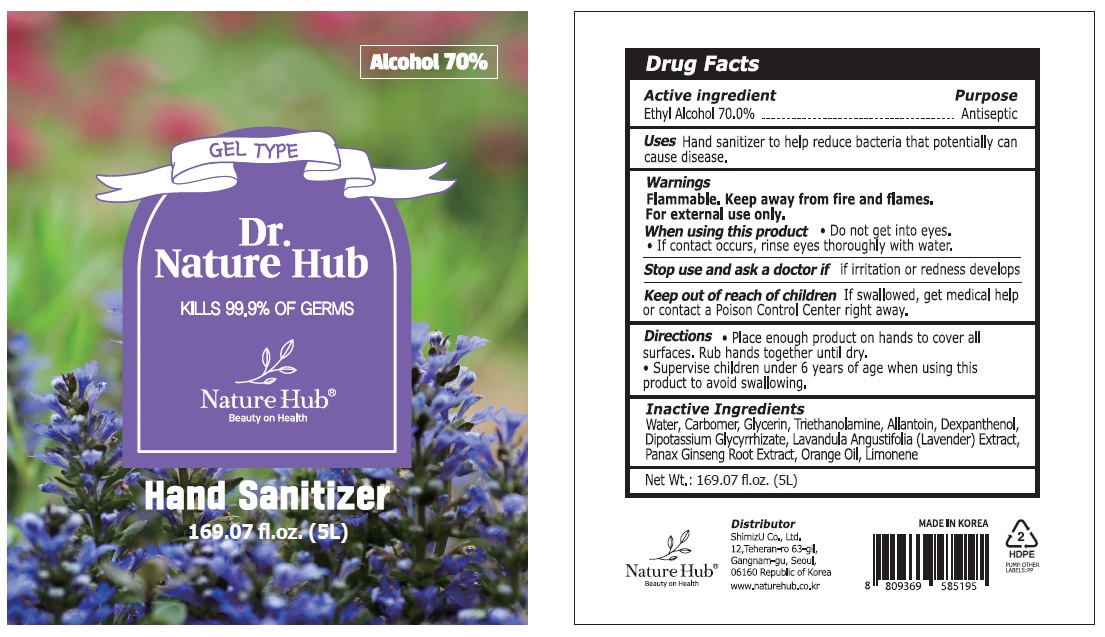 DRUG LABEL: Dr. Nature Hub
NDC: 76901-020 | Form: GEL
Manufacturer: SHIMIZU CO., LTD.
Category: otc | Type: HUMAN OTC DRUG LABEL
Date: 20200604

ACTIVE INGREDIENTS: Alcohol 0.7 L/1 L
INACTIVE INGREDIENTS: WATER; CARBOMER HOMOPOLYMER, UNSPECIFIED TYPE; Glycerin; TROLAMINE; Allantoin; Dexpanthenol; GLYCYRRHIZINATE DIPOTASSIUM; LAVENDER OIL; ASIAN GINSENG; Orange Oil; LIMONENE, (+)-

ACTIVE INGREDIENT

Ethyl Alcohol 70.0%

INACTIVE INGREDIENTS

Carbomer, Glycerin, Triethanolamine, Allantoin, Dexpanthenol, Dipotassium Glycyrrhizate, Lavandula Angustifolia (Lavender) Extract, Panax Ginseng Root Extract, Orange Oil, Limonene, Water

PURPOSE

ANTISEPTIC

WARNINGS

Flammable. Keep away from fire and flames.

For external use only.

When using this product • Do not get into eyes. • If contact occurs, rinse eyes thoroughly with water.

Stop use and ask a doctor if if irritation or redness develops

KEEP OUT OF REACH OF CHILDREN

If swallowed, get medical help or contact a Poison Control Center right away.

Uses

■ Hand sanitizer to help reduce bacteria that potentially can cause disease.

Directions

• Place enough product on hands to cover all surfaces. Rub hands together until dry.

• Supervise children under 6 years of age when using this product to avoid swallowing.